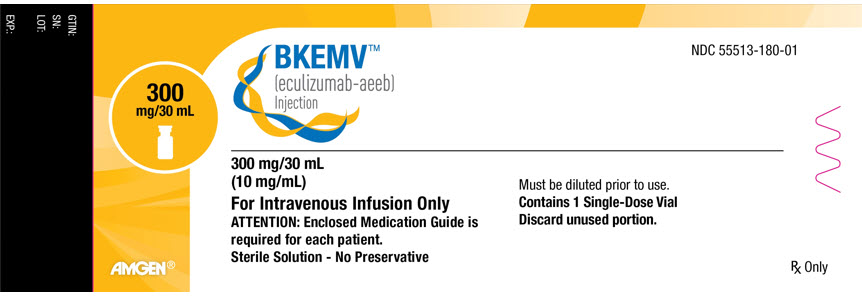 DRUG LABEL: BKEMV
NDC: 55513-180 | Form: INJECTION, SOLUTION, CONCENTRATE
Manufacturer: Amgen Inc
Category: prescription | Type: HUMAN PRESCRIPTION DRUG LABEL
Date: 20251201

ACTIVE INGREDIENTS: ECULIZUMAB 300 mg/30 mL
INACTIVE INGREDIENTS: SORBITOL; ACETIC ACID; POLYSORBATE 80; EDETATE DISODIUM

HIGHLIGHTS OF PRESCRIBING INFORMATION

These highlights do not include all the information needed to use BKEMV safely and effectively. See full prescribing information for BKEMV.
BKEMV® (eculizumab-aeeb) injection, for intravenous use
Initial U.S. Approval: 2024
BKEMV (eculizumab-aeeb) is biosimilar [Biosimilar means that the biological product is approved based on data demonstrating that it is highly similar to an FDA-approved biological product, known as a reference product, and that there are no clinically meaningful differences between the biosimilar product and the reference product. Biosimilarity of BKEMV has been demonstrated for the condition(s) of use (e.g., indication(s), dosing regimen(s)), strength(s), dosage form(s), and route(s) of administration described in its Full Prescribing Information.] to SOLIRIS® (eculizumab).

WARNING: SERIOUS MENINGOCOCCAL INFECTIONS

See full prescribing information for complete boxed warning

Eculizumab products increase the risk of serious and life-threatening infections caused by Neisseria meningitidis.

- Complete or update meningococcal vaccination at least 2 weeks prior to the first dose of BKEMV, unless the risks of delaying BKEMV outweigh the risk of developing a serious infection. Comply with the most current Advisory Committee on Immunization Practices (ACIP) recommendations for meningococcal vaccination in patients receiving a complement inhibitor. (5.1)
- Patients receiving eculizumab products are at increased risk for invasive disease caused by Neisseria meningitidis, even if they develop antibodies following vaccination. Monitor patients for early signs and symptoms of meningococcal infections and evaluate immediately if infection is suspected. (5.1)

BKEMV is available only through a restricted program called BKEMV REMS. (5.2)

RECENT MAJOR CHANGES

Dosage and Administration, (2.3, 2.4, 2.5) | 11/2025

1 INDICATIONS AND USAGE

BKEMV is a complement inhibitor indicated for:

- The treatment of patients with paroxysmal nocturnal hemoglobinuria (PNH) to reduce hemolysis. (1.1)
- The treatment of patients with atypical hemolytic uremic syndrome (aHUS) to inhibit complement-mediated thrombotic microangiopathy. (1.2)
  Limitation of Use
  BKEMV is not indicated for the treatment of patients with Shiga toxin E. coli related hemolytic uremic syndrome (STEC-HUS).
- The treatment of generalized myasthenia gravis (gMG) in adult patients who are anti-acetylcholine receptor (AChR) antibody positive. (1.3)

2 DOSAGE AND ADMINISTRATION

For intravenous infusion only; recommended dosage for:

- PNH: (2.2)
- aHUS and gMG in adults: (2.3)
- aHUS in pediatric patients: (2.4)

3 DOSAGE FORMS AND STRENGTHS

Injection: 300 mg/30 mL (10 mg/mL) in a single-dose vial. (3)

4 CONTRAINDICATIONS

BKEMV is contraindicated for initiation in patients with unresolved serious Neisseria meningitidis infection. (4)

5 WARNINGS AND PRECAUTIONS

- Use caution when administering BKEMV to patients with any other systemic infection. (5.3)
- Infusion-Related Reactions: Monitor patients during infusion, interrupt for reactions, and institute appropriate supportive measures. (5.6)

6 ADVERSE REACTIONS

The most frequently reported adverse reactions in the PNH randomized trial (≥10% overall and greater than placebo) are: headache, nasopharyngitis, back pain, and nausea. (6.1)

The most frequently reported adverse reactions in aHUS single arm prospective trials (≥20%) are: headache, diarrhea, hypertension, upper respiratory infection, abdominal pain, vomiting, nasopharyngitis, anemia, cough, peripheral edema, nausea, urinary tract infections, pyrexia. (6.1)

The most frequently reported adverse reaction in the gMG placebo-controlled clinical trial (≥10%) in adult patients is musculoskeletal pain. (6.1)

To report SUSPECTED ADVERSE REACTIONS, contact Amgen Medical Information at 1-800-77-AMGEN (1-800-772-6436) or FDA at 1-800-FDA-1088 or www.fda.gov/medwatch.

FULL PRESCRIBING INFORMATION

WARNING: SERIOUS MENINGOCOCCAL INFECTIONS

Eculizumab products, complement inhibitors, increase the risk of serious infections caused by Neisseria meningitidis [see Warnings and Precautions (5.1)]. Life-threatening and fatal meningococcal infections have occurred in patients treated with complement inhibitors. These infections may become rapidly life-threatening or fatal if not recognized and treated early.

- Complete or update vaccination for meningococcal bacteria (for serogroups A, C, W, Y, and B) at least 2 weeks prior to the first dose of BKEMV, unless the risks of delaying therapy with BKEMV outweigh the risk of developing a serious infection. Comply with the most current Advisory Committee on Immunization Practices (ACIP) recommendations for vaccinations against meningococcal bacteria in patients receiving a complement inhibitor. See Warnings and Precautions (5.1) for additional guidance on the management of the risk of serious infections caused by meningococcal bacteria.
- Patients receiving eculizumab products are at increased risk for invasive disease caused by Neisseria meningitidis, even if they develop antibodies following vaccination. Monitor patients for early signs and symptoms of serious meningococcal infections and evaluate immediately if infection is suspected.

Because of the risk of serious meningococcal infections, BKEMV is available only through a restricted program under a Risk Evaluation and Mitigation Strategy (REMS) called BKEMV REMS [see Warnings and Precautions (5.2)].

1 INDICATIONS AND USAGE

1.1 Paroxysmal Nocturnal Hemoglobinuria (PNH)

BKEMV is indicated for the treatment of patients with paroxysmal nocturnal hemoglobinuria (PNH) to reduce hemolysis.

1.2 Atypical Hemolytic Uremic Syndrome (aHUS)

BKEMV is indicated for the treatment of patients with atypical hemolytic uremic syndrome (aHUS) to inhibit complement-mediated thrombotic microangiopathy.

Limitation of Use

BKEMV is not indicated for the treatment of patients with Shiga toxin E. coli related hemolytic uremic syndrome (STEC-HUS).

1.3 Generalized Myasthenia Gravis (gMG)

BKEMV is indicated for treatment of generalized myasthenia gravis (gMG) in adult patients who are anti-acetylcholine receptor (AChR) antibody positive.

2 DOSAGE AND ADMINISTRATION

2.1 Recommended Vaccination and Prophylaxis for Meningococcal Infection

Vaccinate patients against meningococcal infection (serogroups A, C, W, Y and B) according to current ACIP recommendations at least 2 weeks prior to initiation of BKEMV [see Warnings and Precautions (5.1)].

If urgent BKEMV therapy is indicated in a patient who is not up to date with meningococcal vaccines according to ACIP recommendations, provide the patient with antibacterial drug prophylaxis and administer these vaccines as soon as possible.

Healthcare providers who prescribe BKEMV must enroll in the BKEMV REMS [see Warnings and Precautions (5.2)].

2.2 Recommended Dosage for Adults – PNH

The recommended dosage of BKEMV for the treatment of PNH in patients 18 years of age and older is administered as an intravenous infusion [see Dosage and Administration (2.7)] as follows:

- 600 mg weekly for the first 4 weeks, followed by
- 900 mg for the fifth dose 1 week later, then
- 900 mg every 2 weeks thereafter.

Administer BKEMV at the recommended dosage regimen time points, or within two days of these time points [see Warnings and Precautions (5.4)].

2.3 Recommended Dosage for Adults – aHUS and gMG

The recommended dosage of BKEMV for the treatment of aHUS and gMG in patients 18 years of age and older is administered as an intravenous infusion [see Dosage and Administration (2.7)] as follows:

- 900 mg weekly for the first 4 weeks, followed by
- 1,200 mg for the fifth dose 1 week later, then
- 1,200 mg every 2 weeks thereafter.

2.4 Recommended Dosage for Pediatric Patients – aHUS

The recommended dosage of BKEMV for the treatment of aHUS in pediatric patients less than 18 years of age is administered as an intravenous infusion based upon body weight, according to the following schedule (Table 1):

Table 1: Dosing Recommendations in Pediatric Patients Less Than 18 Years of Age with aHUS
Patient Body Weight | Induction | Maintenance
40 kg and over | 900 mg weekly for the first 4 weeks | 1,200 mg at week 5; then 1,200 mg every 2 weeks
30 kg to less than 40 kg | 600 mg weekly for the first 2 weeks | 900 mg at week 3; then 900 mg every 2 weeks
20 kg to less than 30 kg | 600 mg weekly for the first 2 weeks | 600 mg at week 3; then 600 mg every 2 weeks
10 kg to less than 20 kg | 600 mg single dose at Week 1 | 300 mg at week 2; then 300 mg every 2 weeks
5 kg to less than 10 kg | 300 mg single dose at Week 1 | 300 mg at week 2; then 300 mg every 3 weeks

Administer BKEMV at the recommended dosage regimen time points, or within two days of these time points.

2.5 Dose Adjustment in Case of Plasmapheresis, Plasma Exchange, Fresh Frozen Plasma Infusion or IVIg

For adult and pediatric patients with aHUS, and adult patients with gMG, supplemental dosing of BKEMV is required in the setting of concomitant plasmapheresis or plasma exchange, or fresh frozen plasma infusion (PE/PI) (Table 2).

Table 2: Supplemental Dose of BKEMV after Plasmapheresis/PE/PI
Type of Plasma Intervention | Most Recent BKEMV Dose | Supplemental BKEMV Dose with Each Plasma Intervention | Timing of Supplemental BKEMV Dose
Plasmapheresis or plasma exchange | 300 mg | 300 mg per each plasmapheresis or plasma exchange session | Within 60 minutes after each plasmapheresis or plasma exchange
Plasmapheresis or plasma exchange | 600 mg or greater | 600 mg per each plasmapheresis or plasma exchange session | Within 60 minutes after each plasmapheresis or plasma exchange
Fresh frozen plasma infusion | 300 mg or greater | 300 mg per infusion of fresh frozen plasma | 60 minutes prior to each infusion of fresh frozen plasma

For patients with gMG, a supplemental dose of BKEMV is required in the setting of concomitant use of intravenous immunoglobulin (IVIg) treatment as described in Table 3.

Table 3: Supplemental Dose of BKEMV with concomitant IVIg
IVIg Frequency | Most Recent BKEMV Dose | Supplemental BKEMV Dose per IVIg Cycle | Timing of Supplemental BKEMV Dose
Acute rescue therapy | No supplemental BKEMV dose needed
Equal to or more frequent than every 4 weeks | 900 mg or more | 600 mg | At the same time as scheduled BKEMV dose
Equal to or more frequent than every 4 weeks | 600 mg or less | 300 mg | At the same time as scheduled BKEMV dose
Less frequent than every 4 weeks | 900 mg or more | 600 mg | At the next scheduled BKEMV dose after the last IVIg cycle
Less frequent than every 4 weeks | 600 mg or less | 300 mg | At the next scheduled BKEMV dose after the last IVIg cycle

2.6 Preparation

Dilute BKEMV to a final admixture concentration of 5 mg/mL using the following steps:

- Withdraw the required amount of BKEMV from the vial into a sterile syringe.
- Transfer the recommended dose to an infusion bag.
- Dilute BKEMV to a final concentration of 5 mg/mL by adding the appropriate amount (equal volume of diluent to drug volume) of 0.9% Sodium Chloride Injection, USP; 0.45% Sodium Chloride Injection, USP; 5% Dextrose in Water Injection, USP; or Ringer's Injection, USP to the infusion bag.

The final admixed BKEMV 5 mg/mL infusion volume is 60 mL for 300 mg doses, 120 mL for 600 mg doses, 180 mL for 900 mg doses or 240 mL for 1,200 mg doses (Table 4).

Table 4: Preparation and Reconstitution of BKEMV
BKEMV Dose | Diluent Volume | Final Volume
300 mg | 30 mL | 60 mL
600 mg | 60 mL | 120 mL
900 mg | 90 mL | 180 mL
1,200 mg | 120 mL | 240 mL

Gently invert the infusion bag containing the diluted BKEMV solution to ensure thorough mixing of the product and diluent. Discard any unused portion left in a vial, as the product contains no preservatives.

Prior to administration, the admixture should be allowed to adjust to room temperature [18°C to 25°C (64°F to 77°F)]. The admixture must not be heated in a microwave or with any heat source other than ambient air temperature.

Parenteral drug products should be inspected visually for particulate matter and discoloration prior to administration, whenever solution and container permit.

2.7 Administration

Only administer as an intravenous infusion.

Do not administer as an intravenous push or bolus injection.

Administer the BKEMV admixture by intravenous infusion over 35 minutes in adults and 1 to 4 hours in pediatric patients via gravity feed, a syringe-type pump, or an infusion pump. Admixed solutions of BKEMV are stable for 64 hours at 2°C to 8°C (36°F to 46°F) or 24 hours at room temperature.

If an adverse reaction occurs during the administration of BKEMV, the infusion may be slowed or stopped at the discretion of the physician. If the infusion is slowed, the total infusion time should not exceed two hours in adults. Monitor the patient for at least one hour following completion of the infusion for signs or symptoms of an infusion-related reaction.

3 DOSAGE FORMS AND STRENGTHS

Injection: 300 mg/30 mL (10 mg/mL) as a clear to opalescent and colorless to slightly yellow solution in a single-dose vial.

4 CONTRAINDICATIONS

BKEMV is contraindicated for initiation in patients with unresolved serious Neisseria meningitidis infection [see Warnings and Precautions (5.1)].

5 WARNINGS AND PRECAUTIONS

5.1 Serious Meningococcal Infections

Eculizumab products, complement inhibitors, increase a patient's susceptibility to serious, life-threatening, or fatal infections caused by meningococcal bacteria (septicemia and/or meningitis) in any serogroup, including non-groupable strains. Life-threatening and fatal meningococcal infections have occurred in both vaccinated and unvaccinated patients treated with complement inhibitors. The initiation of BKEMV treatment is contraindicated in patients with unresolved serious Neisseria meningitidis infection.

Complete or update meningococcal vaccination (for serogroups A, C, W, Y and B) at least 2 weeks prior to administration of the first dose of BKEMV, according to current ACIP recommendations for patients receiving a complement inhibitor. Revaccinate patients in accordance with ACIP recommendations considering the duration of therapy with BKEMV. Note that ACIP recommends an administration schedule in patients receiving complement inhibitors that differs from the administration schedule in the vaccine prescribing information.

If urgent BKEMV therapy is indicated in a patient who is not up to date with meningococcal vaccines according to ACIP recommendations, provide the patient with antibacterial drug prophylaxis and administer meningococcal vaccines as soon as possible. Various durations and regimens of antibacterial drug prophylaxis have been considered, but the optimal durations and drug regimens for prophylaxis and their efficacy have not been studied in unvaccinated or vaccinated patients receiving complement inhibitors, including eculizumab products. The benefits and risks of treatment with BKEMV, as well as the benefits and risks of antibacterial drug prophylaxis in unvaccinated or vaccinated patients, must be considered against the known risks for serious infections caused by Neisseria meningitidis.

Vaccination does not eliminate the risk of serious meningococcal infections, despite development of antibodies following vaccination.

Closely monitor patients for early signs and symptoms of meningococcal infection and evaluate patients immediately if infection is suspected. Inform patients of these signs and symptoms and instruct patients to seek immediate medical care if these signs and symptoms occur. Promptly treat known infections. Meningococcal infection may become rapidly life-threatening or fatal if not recognized and treated early. Consider interruption of BKEMV in patients who are undergoing treatment for serious meningococcal infection, depending on the risks of interrupting treatment in the disease being treated.

BKEMV is available only through a restricted program under a REMS [see Warnings and Precautions (5.2)].

5.2 BKEMV REMS

BKEMV is available only through a restricted program under a REMS called BKEMV REMS, because of the risk of serious meningococcal infections [see Warnings and Precautions (5.1)].

Notable requirements of the BKEMV REMS include the following:

- Prescribers must enroll in the REMS.
- Prescribers must counsel patients about the risk of serious meningococcal infection.
- Prescribers must provide the patients with the REMS educational materials.
- Prescribers must assess patient vaccination status for meningococcal vaccines (against serogroups A, C, W, Y and B) and vaccinate if needed according to current ACIP recommendations 2 weeks prior to the first dose of BKEMV.
- Prescribers must provide a prescription for antibacterial drug prophylaxis if treatment must be started urgently and the patient is not up to date with meningococcal vaccines according to current ACIP recommendations at least two weeks prior to the first dose of BKEMV.
- Healthcare settings and pharmacies that dispense BKEMV must be certified in the REMS and must verify prescribers are certified.
- Patients must receive counseling from the prescriber about the need to receive meningococcal vaccines per ACIP recommendations, the need to take antibiotics as directed by the prescriber, and the signs and symptoms of meningococcal infection.
- Patients must be instructed to carry the Patient Safety Card with them at all times during and for 3 months following treatment with BKEMV.

Further information is available at www.BKEMVREMS.com or 1-866-718-6927.

5.3 Other Infections

Serious infections with Neisseria species (other than Neisseria meningitidis), including disseminated gonococcal infections, have been reported.

Eculizumab products block terminal complement activation; therefore, patients may have increased susceptibility to infections, especially with encapsulated bacteria, such as infections with Neisseria meningitidis but also Streptococcus pneumoniae, Haemophilus influenzae, and to a lesser extent, Neisseria gonorrhoeae. Additionally, Aspergillus infections have occurred in immunocompromised and neutropenic patients. Children treated with eculizumab products may be at increased risk of developing serious infections due to Streptococcus pneumoniae and Haemophilus influenzae type b (Hib). Administer vaccinations for the prevention of Streptococcus pneumoniae and Haemophilus influenzae type b (Hib) infections according to ACIP recommendations. Patients receiving eculizumab products are at increased risk for infections due to these organisms, even if they develop antibodies following vaccination.

5.4 Monitoring Disease Manifestations after BKEMV Discontinuation

Treatment Discontinuation for PNH

Monitor patients after discontinuing BKEMV for at least 8 weeks to detect hemolysis.

Treatment Discontinuation for aHUS

After discontinuing BKEMV, monitor patients with aHUS for signs and symptoms of thrombotic microangiopathy (TMA) complications for at least 12 weeks. In aHUS clinical trials, 18 patients (5 in the prospective studies) discontinued eculizumab treatment. TMA complications occurred following a missed dose in 5 patients, and eculizumab was reinitiated in 4 of these 5 patients.

Clinical signs and symptoms of TMA include changes in mental status, seizures, angina, dyspnea, or thrombosis. In addition, the following changes in laboratory parameters may identify a TMA complication: occurrence of two, or repeated measurement of any one of the following: a decrease in platelet count by 25% or more compared to baseline or the peak platelet count during BKEMV treatment; an increase in serum creatinine by 25% or more compared to baseline or nadir during BKEMV treatment; or, an increase in serum LDH by 25% or more over baseline or nadir during BKEMV treatment.

If TMA complications occur after BKEMV discontinuation, consider reinstitution of BKEMV treatment, plasma therapy [plasmapheresis, plasma exchange, or fresh frozen plasma infusion (PE/PI)], or appropriate organ-specific supportive measures.

5.5 Thrombosis Prevention and Management

The effect of withdrawal of anticoagulant therapy during eculizumab products treatment has not been established. Therefore, treatment with eculizumab products should not alter anticoagulant management.

5.6 Infusion-Related Reactions

Administration of eculizumab products may result in infusion-related reactions, including anaphylaxis or other hypersensitivity reactions. In clinical trials, no patients experienced an infusion-related reaction which required discontinuation of eculizumab. Interrupt BKEMV infusion and institute appropriate supportive measures if signs of cardiovascular instability or respiratory compromise occur.

6 ADVERSE REACTIONS

The following serious adverse reactions are discussed in greater detail in other sections of the labeling:

- Serious Meningococcal Infections [see Warnings and Precautions (5.1)]
- Other Infections [see Warnings and Precautions (5.3)]
- Monitoring Disease Manifestations after BKEMV Discontinuation [see Warnings and Precautions (5.4)]
- Thrombosis Prevention and Management [see Warnings and Precautions (5.5)]
- Infusion-Related Reactions [see Warnings and Precautions (5.6)]

6.1 Clinical Trial Experience

Because clinical trials are conducted under widely varying conditions, adverse reaction rates observed in the clinical trials of a drug cannot be directly compared to rates in the clinical trials of another drug and may not reflect the rates observed in practice.

Meningococcal infections are the most important adverse reactions experienced by patients receiving eculizumab. In PNH clinical studies, two patients experienced meningococcal sepsis. Both patients had previously received a meningococcal vaccine. In clinical studies among patients without PNH, meningococcal meningitis occurred in one unvaccinated patient. Meningococcal sepsis occurred in one previously vaccinated patient enrolled in the retrospective aHUS study during the post-study follow-up period [see Warnings and Precautions (5.1)].

PNH

The data described below reflect exposure to eculizumab in 196 adult patients with PNH, age 18-85, of whom 55% were female. All had signs or symptoms of intravascular hemolysis. Eculizumab was studied in a placebo-controlled clinical study (PNH Study 1, in which 43 patients received eculizumab and 44, placebo); a single arm clinical study (PNH Study 2); and a long-term extension study (E05-001). One hundred and eighty two patients were exposed for greater than one year. All patients received the recommended eculizumab dose regimen.

Table 5 summarizes the adverse reactions that occurred at a numerically higher rate in the eculizumab group than the placebo group and at a rate of 5% or more among patients treated with eculizumab.

Table 5: Adverse Reactions Reported in 5% or More of Eculizumab Treated Patients with PNH and Greater than Placebo in the Controlled Clinical Study
Reaction | Eculizumab (N = 43) N (%) | Placebo (N = 44) N (%)
Headache | 19 (44) | 12 (27)
Nasopharyngitis | 10 (23) | 8 (18)
Back pain | 8 (19) | 4 (9)
Nausea | 7 (16) | 5 (11)
Fatigue | 5 (12) | 1 (2)
Cough | 5 (12) | 4 (9)
Herpes simplex infections | 3 (7) | 0
Sinusitis | 3 (7) | 0
Respiratory tract infection | 3 (7) | 1 (2)
Constipation | 3 (7) | 2 (5)
Myalgia | 3 (7) | 1 (2)
Pain in extremity | 3 (7) | 1 (2)
Influenza-like illness | 2 (5) | 1 (2)

In the placebo-controlled clinical study, serious adverse reactions occurred among 4 (9%) patients receiving eculizumab and 9 (21%) patients receiving placebo. The serious reactions included infections and progression of PNH. No deaths occurred in the study and no patients receiving eculizumab experienced a thrombotic event; one thrombotic event occurred in a patient receiving placebo.

Among 193 patients with PNH treated with eculizumab in the single arm, clinical study or the follow-up study, the adverse reactions were similar to those reported in the placebo-controlled clinical study. Serious adverse reactions occurred among 16% of the patients in these studies. The most common serious adverse reactions were: viral infection (2%), headache (2%), anemia (2%), and pyrexia (2%).

aHUS

The safety of eculizumab therapy in patients with aHUS was evaluated in four prospective, single-arm studies, three in adult and adolescent patients (Studies C08-002A/B, C08-003A/B, and C10-004), one in pediatric and adolescent patients (Study C10-003), and one retrospective study (Study C09-001r).

The data described below were derived from 78 adult and adolescent patients with aHUS in Studies C08-002A/B, C08-003A/B and C10-004. All patients received the recommended dosage of eculizumab. Median exposure was 67 weeks (range: 2-145 weeks). Table 6 summarizes all adverse events reported in at least 10% of patients in Studies C08-002A/B, C08-003A/B and C10-004 combined.

Table 6: Per Patient Incidence of Adverse Events in 10% or More Adult and Adolescent Patients Enrolled in Studies C08-002A/B, C08-003A/B and C10-004 Separately and in Total
 | Number (%) of Patients
 | C08-002A/B (N = 17) | C08-003A/B (N = 20) | C10-004 (N = 41) | Total (N = 78)
Vascular Disorders
Hypertension [includes the preferred terms hypertension, accelerated hypertension, and malignant hypertension.] | 10 (59) | 9 (45) | 7 (17) | 26 (33)
Hypotension | 2 (12) | 4 (20) | 7 (17) | 13 (17)
Infections and Infestations
Bronchitis | 3 (18) | 2 (10) | 4 (10) | 9 (12)
Nasopharyngitis | 3 (18) | 11 (55) | 7 (17) | 21 (27)
Gastroenteritis | 3 (18) | 4 (20) | 2 (5) | 9 (12)
Upper respiratory tract infection | 5 (29) | 8 (40) | 2 (5) | 15 (19)
Urinary tract infection | 6 (35) | 3 (15) | 8 (20) | 17 (22)
Gastrointestinal Disorders
Diarrhea | 8 (47) | 8 (40) | 12 (32) | 29 (37)
Vomiting | 8 (47) | 9 (45) | 6 (15) | 23 (30)
Nausea | 5 (29) | 8 (40) | 5 (12) | 18 (23)
Abdominal pain | 3 (18) | 6 (30) | 6 (15) | 15 (19)
Nervous System Disorders
Headache | 7 (41) | 10 (50) | 15 (37) | 32 (41)
Blood and Lymphatic System Disorders
Anemia | 6 (35) | 7 (35) | 7 (17) | 20 (26)
Leukopenia | 4 (24) | 3 (15) | 5 (12) | 12 (15)
Psychiatric Disorders
Insomnia | 4 (24) | 2 (10) | 5 (12) | 11 (14)
Renal and Urinary Disorders
Renal Impairment | 5 (29) | 3 (15) | 6 (15) | 14 (18)
Proteinuria | 2 (12) | 1 (5) | 5 (12) | 8 (10)
Respiratory, Thoracic and Mediastinal Disorders
Cough | 4 (24) | 6 (30) | 8 (20) | 18 (23)
General Disorders and Administration Site Conditions
Fatigue | 3 (18) | 4 (20) | 3 (7) | 10 (13)
Peripheral edema | 5 (29) | 4 (20) | 9 (22) | 18 (23)
Pyrexia | 4 (24) | 5 (25) | 7 (17) | 16 (21)
Asthenia | 3 (18) | 4 (20) | 6 (15) | 13 (17)
Eye Disorder | 5 (29) | 2 (10) | 8 (20) | 15 (19)
Metabolism and Nutrition Disorders
Hypokalemia | 3 (18) | 2 (10) | 4 (10) | 9 (12)
Neoplasms benign, malignant, and unspecified (including cysts and polyps) | 1 (6) | 6 (30) | 1 (20) | 8 (10)
Skin and Subcutaneous Tissue Disorders
Rash | 2 (12) | 3 (15) | 6 (15) | 11 (14)
Pruritus | 1 (6) | 3 (15) | 4 (10) | 8 (10)
Musculoskeletal and Connective Tissue Disorders
Arthralgia | 1 (6) | 2 (10) | 7 (17) | 10 (13)
Back pain | 3 (18) | 3 (15) | 2 (5) | 8 (10)

In Studies C08-002A/B, C08-003A/B and C10-004 combined, 60% (47/78) of patients experienced a serious adverse event (SAE). The most commonly reported SAEs were infections (24%), hypertension (5%), chronic renal failure (5%), and renal impairment (5%). Five patients discontinued eculizumab due to adverse events; three due to worsening renal function, one due to new diagnosis of Systemic Lupus Erythematosus, and one due to meningococcal meningitis.

Study C10-003 included 22 pediatric and adolescent patients, of which 18 patients were less than 12 years of age. All patients received the recommended dosage of eculizumab. Median exposure was 44 weeks (range: 1 dose-87 weeks).

Table 7 summarizes all adverse events reported in at least 10% of patients enrolled in Study C10-003.

Table 7: Per Patient Incidence of Adverse Reactions in 10% or More Patients Enrolled in Study C10-003
 | 1 month to <12 yrs (N = 18) | Total (N = 22)
Eye Disorders | 3 (17) | 3 (14)
Gastrointestinal Disorders
Abdominal pain | 6 (33) | 7 (32)
Diarrhea | 5 (28) | 7 (32)
Vomiting | 4 (22) | 6 (27)
Dyspepsia | 0 | 3 (14)
General Disorders and Administration Site Conditions
Pyrexia | 9 (50) | 11 (50)
Infections and Infestations
Upper respiratory tract infection | 5 (28) | 7 (32)
Nasopharyngitis | 3 (17) | 6 (27)
Rhinitis | 4 (22) | 4 (18)
Urinary Tract infection | 3 (17) | 4 (18)
Catheter site infection | 3 (17) | 3 (14)
Musculoskeletal and Connective Tissue Disorders
Muscle spasms | 2 (11) | 3 (14)
Nervous System Disorders
Headache | 3 (17) | 4 (18)
Renal and Urinary Disorders | 3 (17) | 4 (18)
Respiratory, Thoracic and Mediastinal Disorders
Cough | 7 (39) | 8 (36)
Oropharyngeal pain | 1 (6) | 3 (14)
Skin and Subcutaneous Tissue Disorders
Rash | 4 (22) | 4 (18)
Vascular Disorders
Hypertension | 4 (22) | 4 (18)

In Study C10-003, 59% (13/22) of patients experienced a serious adverse event (SAE). The most commonly reported SAEs were hypertension (9%), viral gastroenteritis (9%), pyrexia (9%), and upper respiratory infection (9%). One patient discontinued eculizumab due to an adverse event (severe agitation).

Analysis of retrospectively collected adverse event data from pediatric and adult patients enrolled in Study C09-001r (N = 30) revealed a safety profile that was similar to that which was observed in the two prospective studies. Study C09-001r included 19 pediatric patients less than 18 years of age. Overall, the safety of eculizumab in pediatric patients with aHUS enrolled in Study C09-001r appeared similar to that observed in adult patients. The most common (≥15%) adverse events occurring in pediatric patients are presented in Table 8.

Table 8: Adverse Reactions Occurring in at Least 15% of Patients Less than 18 Years of Age Enrolled in Study C09-001r
 | Number (%) of Patients
 | <2 yrs (N = 5) | 2 to <12 yrs (N = 10) | 12 to <18 yrs (N = 4) | Total (N = 19)
General Disorders and Administration Site Conditions
Pyrexia | 4 (80) | 4 (40) | 1 (25) | 9 (47)
Gastrointestinal Disorders
Diarrhea | 1 (20) | 4 (40) | 1 (25) | 6 (32)
Vomiting | 2 (40) | 1 (10) | 1 (25) | 4 (21)
Infections and Infestations
Upper respiratory tract infection [includes the preferred terms upper respiratory tract infection and nasopharyngitis.] | 2 (40) | 3 (30) | 1 (25) | 6 (32)
Respiratory, Thoracic and Mediastinal Disorders
Cough | 3 (60) | 2 (20) | 0 (0) | 5 (26)
Nasal congestion | 2 (40) | 2 (20) | 0 (0) | 4 (21)
Cardiac Disorders
Tachycardia | 2 (40) | 2 (20) | 0 (0) | 4 (21)

Generalized Myasthenia Gravis (gMG)

Adults

In a 26-week placebo-controlled trial evaluating the effect of eculizumab for the treatment of adult patients with gMG (Study ECU-MG-301), 62 patients received eculizumab at the recommended dosage regimen and 63 patients received placebo [see Clinical Studies (14.3)]. Patients were 19 to 79 years of age, and 66% were female. Table 9 displays the most common adverse reactions from gMG Study 1 that occurred in ≥ 5% of eculizumab-treated patients and at a greater frequency than on placebo.

Table 9: Adverse Reactions Reported in 5% or More of Eculizumab-Treated Patients in Study ECU-MG-301 and at a Greater Frequency than in Placebo-Treated Patients
 | Eculizumab (N = 62) N(%) | Placebo (N = 63) N(%)
Gastrointestinal Disorders
Abdominal pain | 5 (8) | 3 (5)
General Disorders and Administration Site Conditions
Peripheral edema | 5 (8) | 3 (5)
Pyrexia | 4 (7) | 2 (3)
Infections and Infestations
Herpes simplex virus infections | 5 (8) | 1 (2)
Injury, Poisoning, and Procedural Complications
Contusion | 5 (8) | 2 (3)
Musculoskeletal and Connective Tissue Disorders
Musculoskeletal pain | 9 (15) | 5 (8)

The most common adverse reactions (≥ 10%) that occurred in eculizumab-treated patients in the long-term extension to Study ECU-MG-301, Study ECU-MG-302, and that are not included in Table 8 were headache (26%), nasopharyngitis (24%), diarrhea (15%), arthralgia (12%), upper respiratory tract infection (11%), and nausea (10%).

6.2 Postmarketing Experience

The following adverse reactions have been identified during post-approval use of eculizumab products. Because these reactions are reported voluntarily from a population of uncertain size, it is not always possible to reliably estimate their frequency or establish a causal relationship to eculizumab products exposure.

Adverse Reactions from Postmarketing Spontaneous Reports

- Fatal or serious infections: Neisseria gonorrhoeae, Neisseria meningitidis, Neisseria sicca/subflava, Neisseria spp unspecified.
- Cases of cholestatic or mixed pattern liver injury with increased serum liver enzymes and bilirubin levels have been reported in adult and pediatric patients with aHUS who were treated with eculizumab products. These events occurred within 3 to 27 days after starting treatment. The median time to resolution (or return to baseline) was approximately 3 weeks.

7 DRUG INTERACTIONS

7.1 Plasmapheresis, Plasma Exchange, Fresh Frozen Plasma Infusion or IVIg

Concomitant use of eculizumab products with plasma exchange (PE), plasmapheresis (PP), fresh frozen plasma infusion (PE/PI), or in patients with gMG on concomitant IVIg treatment can reduce serum eculizumab product concentrations and requires a supplemental dose of BKEMV [see Dosage and Administration (2.5)].

7.2 Neonatal Fc Receptor Blockers

Concomitant use of eculizumab products with neonatal Fc receptor (FcRn) blockers may lower systemic exposures and reduce effectiveness of eculizumab products. Closely monitor for reduced effectiveness of BKEMV.

8 USE IN SPECIFIC POPULATIONS

8.1 Pregnancy

Risk Summary

Limited data on outcomes of pregnancies that have occurred following eculizumab use in pregnant women have not identified a concern for specific adverse developmental outcomes (see Data). There are risks to the mother and fetus associated with untreated paroxysmal nocturnal hemoglobinuria (PNH) and atypical hemolytic uremic syndrome (aHUS) in pregnancy (see Clinical Considerations). Animal studies using a mouse analogue of the eculizumab molecule (murine anti-C5 antibody) showed increased rates of developmental abnormalities and an increased rate of dead and moribund offspring at doses 2-8 times the human dose (see Data).

The estimated background risk of major birth defects and miscarriage for the indicated populations is unknown. All pregnancies have a background risk of birth defect, loss, or other adverse outcomes. In the U.S. general population, the estimated background risk of major birth defect and miscarriage in clinically recognized pregnancies is 2-4% and 15-20%, respectively.

Clinical Considerations

Disease-associated maternal and/or fetal/neonatal risk

PNH in pregnancy is associated with adverse maternal outcomes, including worsening cytopenias, thrombotic events, infections, bleeding, miscarriages and increased maternal mortality, and adverse fetal outcomes, including fetal death and premature delivery.

aHUS in pregnancy is associated with adverse maternal outcomes, including pre-eclampsia and preterm delivery, and adverse fetal/neonatal outcomes, including intrauterine growth restriction (IUGR), fetal death and low birth weight.

Data

Human Data

A pooled analysis of prospectively (50.3%) and retrospectively (49.7%) collected data in more than 300 pregnant women with live births following exposure to eculizumab have not suggested safety concerns. However, these data cannot definitively exclude any drug-associated risk during pregnancy, because of the limited sample size.

Animal Data

Animal reproduction studies were conducted in mice using doses of a murine anti-C5 antibody that approximated 2-4 times (low dose) and 4-8 times (high dose) the recommended human eculizumab dose, based on a body weight comparison. When animal exposure to the antibody occurred in the time period from before mating until early gestation, no decrease in fertility or reproductive performance was observed. When maternal exposure to the antibody occurred during organogenesis, two cases of retinal dysplasia and one case of umbilical hernia were observed among 230 offspring born to mothers exposed to the higher antibody dose; however, the exposure did not increase fetal loss or neonatal death. When maternal exposure to the antibody occurred in the time period from implantation through weaning, a higher number of male offspring became moribund or died (1/25 controls, 2/25 low dose group, 5/25 high dose group). Surviving offspring had normal development and reproductive function.

8.2 Lactation

Risk Summary

Although limited published data does not report detectable levels of eculizumab in human milk, maternal IgG is known to be present in human milk. Available information is insufficient to inform the effect of eculizumab products on the breastfed infant. There are no data on the effects of eculizumab products on milk production. The developmental and health benefits of breastfeeding should be considered along with the mother's clinical need for BKEMV and any potential adverse effects on the breastfed child from BKEMV or from the underlying maternal condition.

8.4 Pediatric Use

PNH

Safety and effectiveness of BKEMV for the treatment of PNH in pediatric patients have not been established.

aHUS

The safety and effectiveness of BKEMV for the treatment of aHUS have been established in pediatric patients. Use of BKEMV in pediatric patients for this indication is supported by evidence from four adequate and well-controlled clinical studies assessing the safety and effectiveness of eculizumab for the treatment of aHUS. The studies included a total of 47 pediatric patients (ages 2 months to 17 years). The safety and effectiveness of eculizumab for the treatment of aHUS appear similar in pediatric and adult patients [see Adverse Reactions (6.1), and Clinical Studies (14.2)].

Vaccinations

Administer vaccinations for the prevention of infection due to Neisseria meningitidis, Streptococcus pneumoniae and Haemophilus influenzae type b (Hib) according to ACIP guidelines [see Warnings and Precautions (5.1, 5.3)].

8.5 Geriatric Use

Fifty-one patients 65 years of age or older (15 with PNH, 4 with aHUS, 26 with gMG, and 6 with another indication) were treated with eculizumab in clinical trials in the approved indications. Although there were no apparent age-related differences observed in these studies, the number of patients aged 65 and over is not sufficient to determine whether they respond differently from younger patients.

11 DESCRIPTION

Eculizumab-aeeb, a complement inhibitor, is a recombinant humanized monoclonal IgG2/4κ antibody produced by Chinese Hamster Ovary (CHO) cell culture and purified by standard bioprocess technology. Eculizumab-aeeb contains human constant regions from human IgG2 sequences and human IgG4 sequences and murine complementarity-determining regions grafted onto the human framework light- and heavy-chain variable regions. Eculizumab-aeeb is composed of two 448 amino acid heavy chains and two 214 amino acid light chains and has a molecular weight of approximately 148 kDa.

BKEMV (eculizumab-aeeb) injection is a sterile, clear to opalescent, colorless to slightly yellow, preservative-free 10 mg/mL solution for intravenous infusion and is supplied in 30 mL single-dose vials. The product is formulated at pH 5.2 and each 30 mL vial contains 300 mg of eculizumab-aeeb, sorbitol (E420) (1500 mg), acetic acid (18.0 mg), polysorbate 80 (3.0 mg) (vegetable origin), edetate disodium (EDTA) (0.6 mg), sodium hydroxide may be added to adjust pH, and Water for Injection, USP.

12 CLINICAL PHARMACOLOGY

12.1 Mechanism of Action

Eculizumab-aeeb, the active ingredient in BKEMV, is a monoclonal antibody that specifically binds to the complement protein C5 with high affinity, thereby inhibiting its cleavage to C5a and C5b and preventing the generation of the terminal complement complex C5b-9.

Eculizumab products inhibit terminal complement-mediated intravascular hemolysis in PNH patients and complement-mediated thrombotic microangiopathy (TMA) in patients with aHUS.

The precise mechanism by which eculizumab exerts its therapeutic effect in gMG patients is unknown, but is presumed to involve reduction of terminal complement complex C5b-9 deposition at the neuromuscular junction.

12.2 Pharmacodynamics

In the placebo-controlled clinical study (PNH Study 1), eculizumab when administered as recommended reduced serum LDH levels from 2200 ± 1034 U/L (mean ± SD) at baseline to 700 ± 388 U/L by week one and maintained the effect through the end of the study at week 26 (327 ± 433 U/L) in patients with PNH. In the single arm clinical study (PNH Study 2), the effect was maintained through week 52 [see Clinical Studies (14)].

In patients with PNH, aHUS, and gMG, free C5 concentrations of <0.5 mcg/mL was correlated with complete blockade of terminal complement activity.

12.3 Pharmacokinetics

Following intravenous maintenance doses of 900 mg once every 2 weeks in patients with PNH, the week 26 observed mean ± SD serum eculizumab maximum concentration (Cmax) was 194 ± 76 mcg/mL and the trough concentration (Ctrough) was 97 ± 60 mcg/mL. Following intravenous maintenance doses of 1,200 mg once every 2 weeks in patients with aHUS, the week 26 observed mean ± SD Ctrough was 242 ± 101 mcg/mL. Following intravenous maintenance doses of 1,200 mg once every 2 weeks in adult patients with gMG, the week 26 observed mean ± SD Cmax was 783 ± 288 mcg/mL and the Ctrough was 341 ± 172 mcg/mL.

Steady state was achieved 4 weeks after starting eculizumab treatment, with accumulation ratio of approximately 2-fold in all studied indications. Population pharmacokinetic analyses showed that eculizumab pharmacokinetics were dose-linear and time-independent over the 600 mg to 1,200 mg dose range, with inter-individual variability of 21% to 38%.

Distribution

The eculizumab volume of distribution for a typical 70 kg patient was 5 L to 8 L.

Elimination

The half-life of eculizumab ranged between 141 hours and 882 hours.

Plasma exchange or infusion increased the clearance of eculizumab by approximately 6.01-fold and reduced the half-life to 90.2 hours. Supplemental dosing is recommended when BKEMV is administered to patients receiving plasma exchange or infusion [see Dosage and Administration (2.5)].

Specific Populations

Age, Sex, and Race:

The pharmacokinetics of eculizumab were not affected by age (2 months to 85 years), sex, or race.

Renal Impairment:

Renal function did not affect the pharmacokinetics of eculizumab in PNH (creatinine clearance of 8 mL/min to 396 mL/min calculated using Cockcroft-Gault formula) or aHUS (estimated glomerular filtration rate [eGFR] of 5 mL/min/1.73 m^2 to 105 mL/min/1.73 m^2 using the Modification of Diet in Renal Disease [MDRD] formula, or gMG patients (eGFR of 44 mL/min/1.73 m^2 to 168 mL/min/1.73 m^2 using MDRD formula).

12.6 Immunogenicity

The observed incidence of anti-drug antibodies is highly dependent on the sensitivity and specificity of the assay. Differences in assay methods preclude meaningful comparisons of the incidence of anti-drug antibodies in the studies described below with the incidence of anti-drug antibodies in other studies, including those of eculizumab or of other eculizumab products.

The immunogenicity of eculizumab has been evaluated using two different immunoassays for the detection of anti-eculizumab antibodies: a direct enzyme-linked immunosorbent assay (ELISA) using the Fab fragment of eculizumab as target was used for the PNH indication; and an electro-chemiluminescence (ECL) bridging assay using the eculizumab whole molecule as target was used for the aHUS, and gMG indications, as well as for additional patients with PNH.

In the PNH population, antibodies to eculizumab were detected in 3/196 (2%) patients using the ELISA assay and in 5/161 (3%) patients using the ECL assay during the entire treatment period. In the aHUS population, antibodies to eculizumab were detected in 3/100 (3%) patients using the ECL assay during the entire treatment period. In the gMG population, none of the 62 adult patients had antibodies to eculizumab detected following the 26-week active treatment.

An ECL based neutralizing assay with a low sensitivity of 2 mcg/mL was performed to detect neutralizing antibodies for the 5 patients with PNH and the 3 patients with aHUS, with anti-eculizumab antibody positive samples using the ECL assay. Two of 161 patients with PNH (1.2%) and 1 of 100 patients with aHUS (1%) had low positive values for neutralizing antibodies.

No apparent correlation of antibody development to clinical response was observed

13 NONCLINICAL TOXICOLOGY

13.1 Carcinogenesis, Mutagenesis, Impairment of Fertility

Long-term animal carcinogenicity studies of eculizumab products have not been conducted.

Genotoxicity studies have not been conducted with eculizumab products.

Effects of eculizumab products upon fertility have not been studied in animals. Intravenous injections of male and female mice with a murine anti-C5 antibody at up to 4-8 times the equivalent of the clinical dose of eculizumab had no adverse effects on mating or fertility.

14 CLINICAL STUDIES

14.1 Paroxysmal Nocturnal Hemoglobinuria (PNH)

The safety and efficacy of eculizumab in PNH patients with hemolysis were assessed in a randomized, double-blind, placebo-controlled 26-week study (PNH Study 1, NCT00122330); PNH patients were also treated with eculizumab in a single arm 52-week study (PNH Study 2, NCT00122304) and in a long-term extension study (E05-001, NCT00122317). Patients received meningococcal vaccination prior to receipt of eculizumab. In all studies, the dose of eculizumab was 600 mg study drug every 7 ± 2 days for 4 weeks, followed by 900 mg 7 ± 2 days later, then 900 mg every 14 ± 2 days for the study duration. Eculizumab was administered as an intravenous infusion over 25 - 45 minutes.

PNH Study 1:

PNH patients with at least four transfusions in the prior 12 months, flow cytometric confirmation of at least 10% PNH cells and platelet counts of at least 100,000/microliter were randomized to either eculizumab (n = 43) or placebo (n = 44). Prior to randomization, all patients underwent an initial observation period to confirm the need for RBC transfusion and to identify the hemoglobin concentration (the "set-point") which would define each patient's hemoglobin stabilization and transfusion outcomes. The hemoglobin set-point was less than or equal to 9 g/dL in patients with symptoms and was less than or equal to 7 g/dL in patients without symptoms. Endpoints related to hemolysis included the numbers of patients achieving hemoglobin stabilization, the number of RBC units transfused, fatigue, and health-related quality of life. To achieve a designation of hemoglobin stabilization, a patient had to maintain a hemoglobin concentration above the hemoglobin set-point and avoid any RBC transfusion for the entire 26-week period. Hemolysis was monitored mainly by the measurement of serum LDH levels, and the proportion of PNH RBCs was monitored by flow cytometry. Patients receiving anticoagulants and systemic corticosteroids at baseline continued these medications.

Major baseline characteristics were balanced (see Table 10).

Table 10: PNH Study 1 Patient Baseline Characteristics
 | Study 1
Parameter | Placebo (N = 44) | eculizumab (N = 43)
Mean age (SD) | 38 (13) | 42 (16)
Gender - female (%) | 29 (66) | 23 (54)
History of aplastic anemia or myelodysplastic syndrome (%) | 12 (27) | 8 (19)
Patients with history of thrombosis (events) | 8 (11) | 9 (16)
Concomitant anticoagulants (%) | 20 (46) | 24 (56)
Concomitant steroids/immunosuppressant treatments (%) | 16 (36) | 14 (33)
Packed RBC units transfused per patient in previous 12 months (median (Q1, Q3)) | 17 (14, 25) | 18 (12, 24)
Mean Hgb level (g/dL) at setpoint (SD) | 8 (1) | 8 (1)
Pre-treatment LDH levels (median, U/L) | 2,234 | 2,032
Free hemoglobin at baseline (median, mg/dL) | 46 | 41

Patients treated with eculizumab had significantly reduced (p< 0.001) hemolysis resulting in improvements in anemia as indicated by increased hemoglobin stabilization and reduced need for RBC transfusions compared to placebo treated patients (see Table 11). These effects were seen among patients within each of the three pre-study RBC transfusion strata (4 - 14 units; 15 - 25 units; >25 units). After 3 weeks of eculizumab treatment, patients reported less fatigue and improved health-related quality of life. Because of the study sample size and duration, the effects of eculizumab products on thrombotic events could not be determined.

Table 11: PNH Study 1 Results
 | Placebo (N = 44) | eculizumab (N = 43)
Percentage of patients with stabilized hemoglobin levels | 0 | 49
Packed RBC units transfused per patient (median) | 10 | 0
(range) | (2 - 21) | (0 - 16)
Transfusion avoidance (%) | 0 | 51
LDH levels at end of study (median, U/L) | 2,167 | 239
Free hemoglobin at end of study (median, mg/dL) | 62 | 5

PNH Study 2 and Extension Study:

PNH patients with at least one transfusion in the prior 24 months and at least 30,000 platelets/microliter received eculizumab over a 52-week period. Concomitant medications included anti-thrombotic agents in 63% of the patients and systemic corticosteroids in 40% of the patients. Overall, 96 of the 97 enrolled patients completed the study (one patient died following a thrombotic event). A reduction in intravascular hemolysis as measured by serum LDH levels was sustained for the treatment period and resulted in a reduced need for RBC transfusion and less fatigue. One hundred and eighty-seven eculizumab-treated PNH patients were enrolled in a long-term extension study. All patients sustained a reduction in intravascular hemolysis over a total eculizumab exposure time ranging from 10 to 54 months. There were fewer thrombotic events with eculizumab treatment than during the same period of time prior to treatment. However, the majority of patients received concomitant anticoagulants; the effects of anticoagulant withdrawal during eculizumab products therapy was not studied [see Warnings and Precautions (5.5)].

14.2 Atypical Hemolytic Uremic Syndrome (aHUS)

Five single-arm studies [four prospective: C08-002A/B (NCT00844545 and NCT00844844), C08-003A/B (NCT00838513 and NCT00844428), C10-003 (NCT01193348), and C10-004 (NCT01194973); and one retrospective: C09-001r (NCT01770951)] evaluated the safety and efficacy of eculizumab for the treatment of aHUS. Patients with aHUS received meningococcal vaccination prior to receipt of eculizumab or received prophylactic treatment with antibiotics until 2 weeks after vaccination. In all studies, the dose of eculizumab in adult and adolescent patients was 900 mg every 7 ± 2 days for 4 weeks, followed by 1,200 mg 7 ± 2 days later, then 1,200 mg every 14 ± 2 days thereafter. The dosage regimen for pediatric patients weighing less than 40 kg enrolled in Study C09-001r and Study C10-003 was based on body weight [see Dosage and Administration (2.3)]. Efficacy evaluations were based on thrombotic microangiopathy (TMA) endpoints.

Endpoints related to TMA included the following:

- platelet count change from baseline
- hematologic normalization (maintenance of normal platelet counts and LDH levels for at least four weeks)
- complete TMA response (hematologic normalization plus at least a 25% reduction in serum creatinine for a minimum of four weeks)
- TMA-event free status (absence for at least 12 weeks of a decrease in platelet count of >25% from baseline, plasma exchange or plasma infusion, and new dialysis requirement)
- Daily TMA intervention rate (defined as the number of plasma exchange or plasma infusion interventions and the number of new dialyses required per patient per day).

aHUS Resistant to PE/PI (Study C08-002A/B)

Study C08-002A/B enrolled patients who displayed signs of thrombotic microangiopathy (TMA) despite receiving at least four PE/PI treatments the week prior to screening. One patient had no PE/PI the week prior to screening because of PE/PI intolerance. In order to qualify for enrollment, patients were required to have a platelet count ≤150 × 10^9/L, evidence of hemolysis such as an elevation in serum LDH, and serum creatinine above the upper limits of normal, without the need for chronic dialysis. The median patient age was 28 (range: 17 to 68 years). Patients enrolled in Study C08-002A/B were required to have ADAMTS13 activity level above 5%; observed range of values in the trial were 70%-121%. Seventy-six percent of patients had an identified complement regulatory factor mutation or auto-antibody. Table 12 summarizes the key baseline clinical and disease-related characteristics of patients enrolled in Study C08-002A/B.

Table 12: Baseline Characteristics of Patients Enrolled in Study C08-002A/B
Parameter | C08-002A/B (N = 17)
Time from aHUS diagnosis until screening in months, median (min, max) | 10 (0.26, 236)
Time from current clinical TMA manifestation until screening in months, median (min, max) | <1 (<1, 4)
Baseline platelet count (× 10^9/L), median (range) | 118 (62, 161)
Baseline LDH (U/L), median (range) | 269 (134, 634)

Patients in Study C08-002A/B received eculizumab for a minimum of 26 weeks. In Study C08-002A/B, the median duration of eculizumab therapy was approximately 100 weeks (range: 2 weeks to 145 weeks).

Renal function, as measured by eGFR, was improved and maintained during eculizumab therapy. The mean eGFR (± SD) increased from 23 ± 15 mL/min/1.73 m^2 at baseline to 56 ± 40 mL/min/1.73 m^2 by 26 weeks; this effect was maintained through 2 years (56 ± 30 mL/min/1.73 m^2). Four of the five patients who required dialysis at baseline were able to discontinue dialysis.

Reduction in terminal complement activity and an increase in platelet count relative to baseline were observed after commencement of eculizumab. Eculizumab reduced signs of complement-mediated TMA activity, as shown by an increase in mean platelet counts from baseline to 26 weeks. In Study C08-002A/B, mean platelet count (± SD) increased from 109 ± 32 × 10^9/L at baseline to 169 ± 72 × 10^9/L by one week; this effect was maintained through 26 weeks (210 ± 68 × 10^9/L), and 2 years (205 ± 46 × 10^9/L). When treatment was continued for more than 26 weeks, two additional patients achieved Hematologic Normalization as well as Complete TMA response. Hematologic Normalization and Complete TMA response were maintained by all responders. In Study C08-002A/B, responses to eculizumab were similar in patients with and without identified mutations in genes encoding complement regulatory factor proteins.

Table 13 summarizes the efficacy results for Study C08-002A/B.

Table 13: Efficacy Results for Study C08-002A/B
Efficacy Parameter | Study C08-002A/B at 26 wks [At data cut-off (September 8, 2010).] (N = 17) | Study C08-002A/B at 2 yrs [At data cut-off (April 20, 2012).] (N = 17)
Complete TMA response, n (%) Median Duration of complete TMA response, weeks (range) | 11 (65) 38 (25, 56) | 13 (77) 99 (25, 139)
eGFR improvement ≥15 mL/min/1.73 m^2, n (%) Median duration of eGFR improvement, days (range) | 9 (53) 251 (70, 392) | 10 (59) ND
Hematologic normalization, n (%) Median Duration of hematologic normalization, weeks (range) | 13 (76) 37 (25, 62) | 15 (88) 99 (25, 145)
TMA event free status, n (%) | 15 (88) | 15 (88)
Daily TMA intervention rate, median (range)
Before eculizumab | 0.82 (0.04, 1.52) | 0.82 (0.04, 1.52)
On eculizumab treatment | 0 (0, 0.31) | 0 (0, 0.36)

aHUS Sensitive to PE/PI (Study C08-003A/B)

Study C08003A/B enrolled patients undergoing chronic PE/PI who generally did- not display hematologic signs of ongoing thrombotic microangiopathy (TMA). All patients had received PT at least once every two weeks, but no more than three times per week, for a minimum of eight weeks prior to the first eculizumab dose. Patients on chronic dialysis were permitted to enroll in Study C08-003A/B. The median patient age was 28 years (range: 13 to 63 years). Patients enrolled in Study C08003A/B were required to have ADAMTS13 activity level above 5%; observed-range of values in the trial were 37%-118%. Seventy percent of patients had an identified complement regulatory factor mutation or auto-antibody. Table 14 summarizes the key baseline clinical and disease related- characteristics of patients enrolled in Study C08-003A/B.

Table 14: Baseline Characteristics of Patients Enrolled in Study C08-003A/B
Parameter | Study C08-003A/B (N = 20)
Time from aHUS diagnosis until screening in months, median (min, max) | 48 (0.66, 286)
Time from current clinical TMA manifestation until screening in months, median (min, max) | 9 (1, 45)
Baseline platelet count (× 10^9/L), median (range) | 218 (105, 421)
Baseline LDH (U/L), median (range) | 200 (151, 391)

Patients in Study C08-003A/B received eculizumab for a minimum of 26 weeks. In Study C08-003A/B, the median duration of eculizumab therapy was approximately 114 weeks (range: 26 to 129 weeks).

Renal function, as measured by eGFR, was maintained during eculizumab therapy. The mean eGFR (± SD) was 31 ± 19 mL/min/1.73 m^2 at baseline, and was maintained through 26 weeks (37 ± 21 mL/min/1.73 m^2) and 2 years (40 ± 18 mL/min/1.73 m^2). No patient required new dialysis with eculizumab.

Reduction in terminal complement activity was observed in all patients after the commencement of eculizumab. Eculizumab reduced signs of complement-mediated TMA activity, as shown by an increase in mean platelet counts from baseline to 26 weeks. Platelet counts were maintained at normal levels despite the elimination of PE/PI. The mean platelet count (± SD) was 228 ± 78 × 10^9/L at baseline, 233 ± 69 × 10^9/L at week 26, and 224 ± 52 × 10^9/L at 2 years. When treatment was continued for more than 26 weeks, six additional patients achieved Complete TMA response. Complete TMA Response and Hematologic Normalization were maintained by all responders. In Study C08-003A/B, responses to eculizumab were similar in patients with and without identified mutations in genes encoding complement regulatory factor proteins.

Table 15 summarizes the efficacy results for Study C08-003A/B.

Table 15: Efficacy Results for Study C08-003A/B
Efficacy Parameter | Study C08-003A/B at 26 wks [At data cut-off (September 8, 2010).] (N = 20) | Study C08-003A/B at 2 yrs [At data cut-off (April 20, 2012).] (N = 20)
Complete TMA response, n (%) Median duration of complete TMA response, weeks (range) | 5 (25) 32 (12, 38) | 11 (55) 68 (38, 109)
eGFR improvement ≥15 mL/min/1.73 m^2, n (%) | 1 (5) | 8 (40)
TMA Event free status n (%) | 16 (80) | 19 (95)
Daily TMA intervention rate, median (range)
Before eculizumab | 0.23 (0.05, 1.07) | 0.23 (0.05, 1.07)
On eculizumab treatment | 0 | 0 (0, 0.01)
Hematologic normalization [In Study C08-003A/B, 85% of patients had normal platelet counts and 80% of patients had normal serum LDH levels at baseline, so hematologic normalization in this population reflects maintenance of normal parameters in the absence of PE/PI.] , n (%) Median duration of hematologic normalization, weeks (range) [Calculated at each post-dose day of measurement (excluding Days 1 to 4) using a repeated measurement ANOVA model.] | 18 (90) 38 (22, 52) | 18 (90) 114 (33, 125)

Retrospective Study in Patients with aHUS (C09-001r)

The efficacy results for the aHUS retrospective study (Study C09-001r) were generally consistent with results of the two prospective studies. Eculizumab reduced signs of complement-mediated TMA activity, as shown by an increase in mean platelet counts from baseline. Mean platelet count (± SD) increased from 171 ± 83 × 10^9/L at baseline to 233 ±10^9 × 10^9/L after one week of therapy; this effect was maintained through 26 weeks (mean platelet count (± SD) at week 26: 254 ± 79 × 10^9/L).

A total of 19 pediatric patients (ages 2 months to 17 years) received eculizumab in Study C09-001r. The median duration of eculizumab therapy was 16 weeks (range 4 to 70 weeks) for children < 2 years of age (n = 5), 31 weeks (range 19 to 63 weeks) for children 2 to <12 years of age (n = 10), and 38 weeks (range 1 to 69 weeks) for patients 12 to < 18 years of age (n = 4). Fifty-three percent of pediatric patients had an identified complement regulatory factor mutation or auto-antibody.

Overall, the efficacy results for these pediatric patients appeared consistent with what was observed in patients enrolled in Studies C08-002A/B and C08-003A/B (Table 16). No pediatric patient required new dialysis during treatment with eculizumab.

Table 16: Efficacy Results in Pediatric Patients Enrolled in Study C09-001r
Efficacy Parameter | <2 yrs (N = 5) | 2 to <12 yrs (N = 10) | 12 to <18 yrs (N = 4) | Total (N = 19)
Complete TMA response, n (%) | 2 (40) | 5 (50) | 1 (25) | 8 (42)
Patients with eGFR improvement ≥ 15 mL/min/1.73 m^2, n (%) [Of the 9 patients who experienced an eGFR improvement of at least 15 mL/min/1.73 m^2, one received dialysis throughout the study period and another received eculizumab as prophylaxis following renal allograft transplantation.] | 2 (40) | 6 (60) | 1 (25) | 9 (47)
Platelet count normalization, n (%) [Platelet count normalization was defined as a platelet count of at least 150,000 × 10^9/L on at least two consecutive measurements spanning a period of at least 4 weeks.] | 4 (80) | 10 (100) | 3 (75) | 17 (89)
Hematologic Normalization, n (%) | 2 (40) | 5 (50) | 1 (25) | 8 (42)
Daily TMA intervention rate, median (range)
Before eculizumab | 1 (0, 2) | <1 (0.07, 1.46) | <1 (0, 1) | 0.31 (0.00, 2.38)
On eculizumab treatment | <1 (0, <1) | 0 (0, <1) | 0 (0, <1) | 0.00 (0.00 , 0.08)

Adult Patients with aHUS (Study C10-004)

Study C10-004 enrolled patients who displayed signs of thrombotic microangiopathy (TMA). In order to qualify for enrollment, patients were required to have a platelet count < lower limit of normal range (LLN), evidence of hemolysis such as an elevation in serum LDH, and serum creatinine above the upper limits of normal, without the need for chronic dialysis. The median patient age was 35 (range: 18 to 80 years). All patients enrolled in Study C10-004 were required to have ADAMTS13 activity level above 5%; observed range of values in the trial were 28%-116%. Fifty-one percent of patients had an identified complement regulatory factor mutation or auto-antibody. A total of 35 patients received PE/PI prior to eculizumab. Table 17 summarizes the key baseline clinical and disease-related characteristics of patients enrolled in Study C10-004.

Table 17: Baseline Characteristics of Patients Enrolled in Study C10-004
Parameter | Study C10-004 (N = 41)
Time from aHUS diagnosis until start of study drug in months, median (range) | 0.79 (0.03 – 311)
Time from current clinical TMA manifestation until first study dose in months, median (range) | 0.52 (0.03 – 19)
Baseline platelet count (× 10^9/L), median (range) | 125 (16 – 332)
Baseline LDH (U/L), median (range) | 375 (131 – 3318)

Patients in Study C10-004 received eculizumab for a minimum of 26 weeks. In Study C10-004, the median duration of eculizumab therapy was approximately 50 weeks (range: 13 weeks to 86 weeks).

Renal function, as measured by eGFR, was improved during eculizumab therapy. The mean eGFR (± SD) increased from 17 ± 12 mL/min/1.73 m^2 at baseline to 47 ± 24 mL/min/1.73 m^2 by 26 weeks. Twenty of the 24 patients who required dialysis at study baseline were able to discontinue dialysis during eculizumab treatment.

Reduction in terminal complement activity and an increase in platelet count relative to baseline were observed after commencement of eculizumab. Eculizumab reduced signs of complement-mediated TMA activity, as shown by an increase in mean platelet counts from baseline to 26 weeks. In Study C10-004, mean platelet count (± SD) increased from 119 ± 66 × 10^9/L at baseline to 200 ± 84 × 10^9/L by one week; this effect was maintained through 26 weeks (mean platelet count (± SD) at week 26: 252 ± 70 × 10^9/L). In Study C10-004, responses to eculizumab were similar in patients with and without identified mutations in genes encoding complement regulatory factor proteins or auto-antibodies to factor H.

Table 18 summarizes the efficacy results for Study C10-004.

Table 18: Efficacy Results for Study C10-004
Efficacy Parameter | Study C10-004 (N = 41)
Complete TMA response, n (%), 95% CI Median duration of complete TMA response, weeks (range) | 23 (56) 40,72 42 (6, 75)
Patients with eGFR improvement ≥15 mL/min/1.73 m^2, n (%) | 22 (54)
Hematologic Normalization, n (%) Median duration of hematologic normalization, weeks (range) | 36 (88) 46 (10, 75)
TMA Event free Status, n (%) | 37 (90)
Daily TMA Intervention Rate, median (range)
Before eculizumab | 0.63 (0, 1.38)
On eculizumab treatment | 0 (0, 0.58)

Pediatric and Adolescent Patients with aHUS (Study C10-003)

Study C10-003 enrolled patients who were required to have a platelet count < lower limit of normal range (LLN), evidence of hemolysis such as an elevation in serum LDH above the upper limits of normal, serum creatinine level ≥ 97 percentile for age without the need for chronic dialysis. The median patient age was 6.5 (range: 5 months to 17 years). Patients enrolled in Study C10-003 were required to have ADAMTS13 activity level above 5%; observed range of values in the trial were 38%-121%. Fifty percent of patients had an identified complement regulatory factor mutation or auto-antibody. A total of 10 patients received PE/PI prior to eculizumab. Table 19 summarizes the key baseline clinical and disease-related characteristics of patients enrolled in Study C10-003.

Table 19: Baseline Characteristics of Patients Enrolled in Study C10-003
Parameter | Patients 1 month to <12 years (N = 18) | All Patients (N = 22)
Time from aHUS diagnosis until start of study drug in months, median (range) | 0.51 (0.03-58) | 0.56 (0.03-191)
Time from current clinical TMA manifestation until first study dose in months, median (range) | 0.23 (0.03-4) | 0.2 (0.03-4)
Baseline platelet count (× 10^9/L), median (range) | 110 (19-146) | 91 (19-146)
Baseline LDH (U/L) median (range) | 1510 (282-7164) | 1244 (282-7164)

Patients in Study C10-003 received eculizumab for a minimum of 26 weeks. In Study C10-003, the median duration of eculizumab therapy was approximately 44 weeks (range: 1 dose to 88 weeks).

Renal function, as measured by eGFR, was improved during eculizumab therapy. The mean eGFR (± SD) increased from 33 ± 30 mL/min/1.73 m^2 at baseline to 98 ± 44 mL/min/1.73 m^2 by 26 weeks. Among the 20 patients with a CKD stage ≥2 at baseline, 17 (85%) achieved a CKD improvement of ≥1 stage. Among the 16 patients ages 1 month to <12 years with a CKD stage ≥2 at baseline, 14 (88%) achieved a CKD improvement by ≥1 stage. Nine of the 11 patients who required dialysis at study baseline were able to discontinue dialysis during eculizumab treatment. Responses were observed across all ages from 5 months to 17 years of age.

Reduction in terminal complement activity was observed in all patients after commencement of eculizumab. Eculizumab reduced signs of complement-mediated TMA activity, as shown by an increase in mean platelet counts from baseline to 26 weeks. The mean platelet count (± SD) increased from 88 ± 42 × 10^9/L at baseline to 281 ± 123 × 10^9/L by one week; this effect was maintained through 26 weeks (mean platelet count (±SD) at week 26: 293 ± 106 × 10^9/L). In Study C10-003, responses to eculizumab were similar in patients with and without identified mutations in genes encoding complement regulatory factor proteins or auto-antibodies to factor H.

Table 20 summarizes the efficacy results for Study C10-003.

Table 20: Efficacy Results for Study C10-003
Efficacy Parameter | Patients 1 month to <12 years (N = 18) | All Patients (N = 22)
Complete TMA response, n (%) | 11 (61) | 14 (64)
95% CI | 36, 83 | 41, 83
Median Duration of complete TMA response, weeks (range) [Through data cutoff (October 12, 2012).] | 40 (14, 77) | 37 (14, 77)
eGFR improvement ≥15 mL/min/1.73∙m^2∙n (%) | 16 (89) | 19 (86)
Complete Hematologic Normalization, n (%) | 14 (78) | 18 (82)
Median Duration of complete hematologic normalization, weeks (range) | 38 (14, 77) | 38 (14, 77)
TMA Event-Free Status, n (%) | 17 (94) | 21 (95)
Daily TMA Intervention rate, median (range)
Before eculizumab treatment | 0.2 (0, 1.7) | 0.4 (0, 1.7)
On eculizumab treatment | 0 (0, 0.01) | 0 (0, 0.01)

14.3 Generalized Myasthenia Gravis (gMG)

The efficacy of eculizumab for the treatment of gMG was established in Study ECU-MG-301 (NCT01997229), a 26-week randomized, double-blind, parallel-group, placebo-controlled, multi-center trial that enrolled adult patients who met the following criteria at screening:

1. Positive serologic test for anti-AChR antibodies,
2. Myasthenia Gravis Foundation of America (MGFA) Clinical Classification Class II to IV,
3. MG-Activities of Daily Living (MG-ADL) total score ≥ 6,
4. Failed treatment over 1 year or more with 2 or more immunosuppressive therapies (ISTs) either in combination or as monotherapy, or failed at least 1 IST and required chronic plasmapheresis or plasma exchange (PE) or intravenous immunoglobulin (IVIg).

A total of 62 patients were randomized to receive eculizumab treatment and 63 were randomized to receive placebo. Baseline characteristics were similar between treatment groups, including age at diagnosis (38 years in each group), gender [66% female (eculizumab) versus 65% female (placebo)], and duration of gMG [9.9 (eculizumab) versus 9.2 (placebo) years]. Over 95% of patients in each group were receiving acetylcholinesterase (AChE) inhibitors, and 98% were receiving immunosuppressant therapies (ISTs). Approximately 50% of each group had been previously treated with at least 3 ISTs.

Eculizumab was administered according to the recommended dosage regimen [see Dosage and Administration (2.4)].

The primary efficacy endpoint for Study ECU-MG-301 was a comparison of the change from baseline between treatment groups in the Myasthenia Gravis-Specific Activities of Daily Living scale (MG-ADL) total score at Week 26. The MG-ADL is a categorical scale that assesses the impact on daily function of 8 signs or symptoms that are typically affected in gMG. Each item is assessed on a 4-point scale where a score of 0 represents normal function and a score of 3 represents loss of ability to perform that function (total score 0-24). A statistically significant difference favoring eculizumab was observed in the mean change from baseline to Week 26 in MG-ADL total scores [-4.2 points in the eculizumab-treated group compared with -2.3 points in the placebo-treated group (p = 0.006)].

A key secondary endpoint in Study ECU-MG-301 was the change from baseline in the Quantitative Myasthenia Gravis (QMG) total score at Week 26. The QMG is a 13-item categorical scale assessing muscle weakness. Each item is assessed on a 4-point scale where a score of 0 represents no weakness and a score of 3 represents severe weakness (total score 0-39). A statistically significant difference favoring eculizumab was observed in the mean change from baseline to Week 26 in QMG total scores [-4.6 points in the eculizumab-treated group compared with -1.6 points in the placebo-treated group (p = 0.001)].

The results of the analysis of the MG-ADL and QMG from Study ECU-MG-301 are shown in Table 21.

Table 21: Analysis of Change from Baseline to Week 26 in MG-ADL and QMG Total Scores in Study ECU-MG-301
Efficacy Endpoints | Eculizumab-LS Mean (N = 62) | Placebo-LS Mean (N = 63) | Eculizumab change relative to placebo – LS Mean Difference | p-values
 | (SEM) | (SEM) | (95% CI)
MG-ADL | −4.2 (0.49) | −2.3 (0.48) | −1.9 (-3.3, −0.6) | (0.006 [in least square means at Week 26 using a repeated measure analysis;] , 0.014 [in ranks at Week 26 using a worst rank analysis)])
QMG | −4.6 (0.60) | −1.6 (0.59) | −3.0 (-4.6, −1.3) | (0.001, 0.005)
SEM= Standard Error of the Mean;
Eculizumab-LSMean = least square mean for the treatment group;
Placebo-LSMean = least square mean for the placebo group;
LSMean-Difference (95% CI) = Difference in least square mean with 95% confidence interval;
p-values (testing the null hypothesis that there is no difference between the two treatment arms

In Study ECU-MG-301, a clinical response was defined in the MG-ADL total score as at least a 3-point improvement and in QMG total score as at least a 5-point improvement. The proportion of clinical responders at Week 26 with no rescue therapy was statistically significantly higher for eculizumab compared to placebo for both measures. For both endpoints, and also at higher response thresholds (≥ 4-, 5-, 6-, 7-, or 8-point improvement on MG-ADL, and ≥ 6-, 7-, 8-, 9-, or 10-point improvement on QMG), the proportion of clinical responders was consistently greater for eculizumab compared to placebo. Available data suggest that clinical response is usually achieved by 12 weeks of eculizumab treatment.

16 HOW SUPPLIED/STORAGE AND HANDLING

BKEMV (eculizumab-aeeb) injection is a sterile, preservative-free, clear to opalescent, colorless to slightly yellow solution supplied as one 300 mg/30 mL (10 mg/mL) single-dose vial per carton (NDC 55513-180-01).

STORAGE AND HANDLING

Store BKEMV vials refrigerated at 2°C to 8°C (36°F to 46°F) in the original carton to protect from light until time of use. BKEMV vials may be stored in the original carton at controlled room temperature [not more than 25°C (77°F)] for only a single period up to 7 days. Do not use beyond the expiration date stamped on the carton. Refer to Dosage and Administration (2) for information on the stability and storage of diluted solutions of BKEMV.

DO NOT FREEZE. DO NOT SHAKE.

17 PATIENT COUNSELING INFORMATION

Advise the patients and/or caregivers to read the FDA-approved patient labeling (Medication Guide).

Serious Meningococcal Infections

Advise patients of the risk of serious meningococcal infection.

Inform patients of the need to complete or update their meningococcal vaccinations at least 2 weeks prior to receiving the first dose of BKEMV or receive antibacterial drug prophylaxis if BKEMV treatment must be initiated immediately and they have not been previously vaccinated. Inform patients of the requirement to be revaccinated according to current ACIP recommendations for meningococcal infection while on BKEMV therapy [see Warnings and Precautions (5.1)].

Inform patients that vaccination may not prevent serious meningococcal infection and to seek immediate medical attention if the following signs or symptoms occur [see Warnings and Precautions (5.1)]:

- fever
- fever and a rash
- fever with high heart rate
- headache with nausea or vomiting
- headache and a fever
- headache with a stiff neck or stiff back
- confusion
- muscle aches with flu-like symptoms
- eyes sensitive to light

Inform patients that they will be given a Patient Safety Card for BKEMV that they should carry with them at all times during and for 3 months following treatment with BKEMV. This card describes symptoms which, if experienced, should prompt the patient to immediately seek medical evaluation.

BKEMV REMS

BKEMV is available only through a restricted program called BKEMV REMS [see Warnings and Precautions (5.2)].

Inform the patient of the following notable requirements:

- Patients must receive counseling about the risk of serious meningococcal infections.
- Patients must receive written educational materials about this risk.
- Patients must be instructed to carry the Patient Safety Card with them at all times during and for 3 months following treatment with BKEMV.
- Patients must be instructed to complete or update meningococcal vaccines for serogroups A, C, W, Y and B per ACIP recommendations as directed by the prescriber prior to treatment with BKEMV.
- Patients must receive antibiotics as directed by the prescriber if they are not up to date with meningococcal vaccines and have to start BKEMV right away.

Other Infections

Counsel patients about gonorrhea prevention and advise regular testing for patients at-risk.

Inform patients that there may be an increased risk of other types of infections, particularly those due to encapsulated bacteria.

Aspergillus infections have occurred in immunocompromised and neutropenic patients.

Inform parents or caregivers of children receiving BKEMV for the treatment of aHUS that their child should be vaccinated against Streptococcus pneumoniae and Haemophilus influenzae type b (Hib) according to current medical guidelines.

Infusion-Related Reactions

Advise patients that administration of BKEMV may result in infusion-related reactions.

Discontinuation

Inform patients with PNH that they may develop serious hemolysis due to PNH when BKEMV is discontinued and that they will be monitored by their healthcare professional for at least 8 weeks following BKEMV discontinuation.

Inform patients with aHUS that there is a potential for TMA complications due to aHUS when BKEMV is discontinued and that they will be monitored by their healthcare professional for at least 12 weeks following BKEMV discontinuation. Inform patients who discontinue BKEMV to keep the Patient Safety Card with them for three months after the last BKEMV dose, because the increased risk of meningococcal infection persists for several weeks following discontinuation of BKEMV.

BKEMV® (eculizumab-aeeb)

Manufactured by:
Amgen Inc.
One Amgen Center Drive
Thousand Oaks, CA 91320-1799

U.S. License Number 1080

AMGEN and BKEMV (eculizumab-aeeb) are trademarks owned or licensed by Amgen Inc., its subsidiaries, or affiliates.

© 2024-2025 Amgen Inc. All rights reserved.

1xxxxxx-v3

MEDICATION GUIDE
BKEMV® (bee-KEM-vee)
(eculizumab-aeeb)
injection, for intravenous use

What is the most important information I should know about BKEMV?
BKEMV is a medicine that affects your immune system. BKEMV may lower the ability of your immune system to fight infections.

- BKEMV increases your chance of getting serious meningococcal infections caused by Neisseria meningitidis bacteria. Meningococcal infections may quickly become life-threatening or cause death if not recognized and treated early.
  - You must complete or update your meningococcal vaccine(s) at least 2 weeks before your first dose of BKEMV.
  - If you have not completed your meningococcal vaccines and BKEMV must be started right away, you should receive the required vaccine(s) as soon as possible.
  - If you have not been vaccinated and BKEMV must be started right away, you should also receive antibiotics to take for as long as your healthcare provider tells you.
  - If you had a meningococcal vaccine in the past, you might need additional vaccines before starting BKEMV. Your healthcare provider will decide if you need additional meningococcal vaccines.
  - Meningococcal vaccines do not prevent all meningococcal infections. Call your healthcare provider or get emergency medical care right away if you get any of these signs and symptoms of a serious meningococcal infection:

- fever
- fever with high heart rate
- headache and fever
- confusion
- muscle aches with flu-like symptoms

- fever and a rash
- headache with nausea or vomiting
- headache with a stiff neck or stiff back
- eyes sensitive to light

Your healthcare provider will give you a Patient Safety Card about the risk of serious meningococcal infection. Carry it with you at all times during treatment and for 3 months after your last dose of BKEMV. Your risk of meningococcal infection may continue for several weeks after your last dose of BKEMV. It is important to show this card to any healthcare provider who treats you. This will help them diagnose and treat you quickly.

BKEMV is only available through a program called the BKEMV Risk Evaluation and Mitigation Strategy (REMS). Before you can receive BKEMV, your healthcare provider must:

- enroll in the BKEMV REMS program
- counsel you about the risk of serious meningococcal infections
- give you information about the signs and symptoms of serious meningococcal infection
- make sure that you are vaccinated against serious infections caused by meningococcal bacteria and that you receive antibiotics if you need to start BKEMV right away and you are not up to date on your vaccines.
- give you a Patient Safety Card about your risk of meningococcal infection, as discussed above

BKEMV may also increase the risk of other types of serious infections caused by encapsulated bacteria, including Streptococcus pneumoniae, Haemophilus influenzae, and Neisseria gonorrhoeae.

- If your child is treated with BKEMV, your child should receive vaccines against Streptococcus pneumoniae and Haemophilus influenzae type b (Hib).
- Certain people may be at risk of serious infections with gonorrhea. Talk to your healthcare provider about whether you are at risk for gonorrhea infection, about gonorrhea prevention, and regular testing.
- Certain fungal infections (aspergillus) may also happen if you take BKEMV and have a weak immune system or a low white blood cell count.

For more information about side effects, see "What are the possible side effects of BKEMV?"

What is BKEMV?
BKEMV is a prescription medicine used to treat:

- people with paroxysmal nocturnal hemoglobinuria (PNH).
- people with atypical hemolytic uremic syndrome (aHUS). BKEMV is not for use in treating people with Shiga toxin E. coli related hemolytic uremic syndrome (STEC-HUS).
- adults with generalized myasthenia gravis (gMG) who are anti-acetylcholine receptor (AChR) antibody positive.

It is not known if BKEMV is safe and effective in children with PNH.

Who should not receive BKEMV?
Do not receive BKEMV if you have a serious meningococcal infection when you are starting BKEMV treatment.

Before you receive BKEMV, tell your healthcare provider about all of your medical conditions, including if you:

- have an infection or fever.
- are pregnant or plan to become pregnant. It is not known if BKEMV will harm your unborn baby.
- are breastfeeding or plan to breastfeed. It is not known if BKEMV passes into your breast milk.

Tell your healthcare provider about all the medicines you take, including prescription and over-the-counter medicines, vitamins, and herbal supplements. BKEMV and other medicines can affect each other causing side effects.
Know the medications you take and the vaccines you receive. Keep a list of them to show your healthcare provider and pharmacist when you get a new medicine.

How should I receive BKEMV?

- Your healthcare provider will give you BKEMV into your vein through an intravenous (IV) line usually over 35 minutes in adults and 1 to 4 hours in children.
- Adults will usually receive a BKEMV infusion:
  - weekly for 5 weeks, then
  - every 2 weeks.
- Children less than 18 years of age, your healthcare provider will decide how often you will receive BKEMV depending on your age and body weight.
- After each infusion, you should be monitored for at least 1 hour for infusion-related reactions. See "What are the possible side effects of BKEMV?" If you have an infusion-related reaction during your BKEMV infusion, your healthcare provider may decide to give BKEMV more slowly or stop your infusion.
- If you miss a BKEMV infusion, call your healthcare provider right away.
- If you have PNH, your healthcare provider will need to monitor you closely for at least 8 weeks after stopping BKEMV. Stopping treatment with BKEMV may cause breakdown of your red blood cells due to PNH.
  Symptoms or problems that can happen due to red blood cell breakdown include:

- drop in the number of your red blood cell count
- kidney problems

- drop in your platelet counts
- blood clots

- confusion
- difficulty breathing
- chest pain

- If you have aHUS, your healthcare provider will need to monitor you closely for at least 12 weeks after stopping BKEMV for signs of worsening aHUS symptoms or problems related to abnormal clotting (thrombotic microangiopathy).
  Symptoms or problems that can happen with abnormal clotting may include:

- stroke
- difficulty breathing

- confusion
- kidney problems

- seizure
- swelling in arms or legs

- chest pain (angina)
- a drop in your platelet count

What are the possible side effects of BKEMV?
BKEMV can cause serious side effects including:

- See "What is the most important information I should know about BKEMV?"
- Serious infusion-related reactions. Serious infusion-related reactions can happen during your BKEMV infusion. Tell your healthcare provider or nurse right away if you get any of these symptoms during your BKEMV infusion:

- chest pain
- trouble breathing or shortness of breath

- swelling of your face, tongue, or throat
- feel faint or pass out

If you have an infusion-related reaction to BKEMV, your healthcare provider may need to infuse BKEMV more slowly or stop BKEMV. See "How should I receive BKEMV?"

The most common side effects in people with PNH treated with BKEMV include:

- headache
- pain or swelling of your nose or throat (nasopharyngitis)

- back pain
- nausea

The most common side effects in people with aHUS treated with BKEMV include:

- headache
- diarrhea
- high blood pressure (hypertension)
- common cold (upper respiratory infection)

- stomach-area (abdominal pain)
- vomiting
- pain or swelling of your nose or throat (nasopharyngitis)

- low red blood cell count (anemia)
- cough
- swelling of legs or feet (peripheral edema)

- nausea
- urinary tract infections
- fever

The most common side effects in people with gMG treated with BKEMV include:

- muscle and joint (musculoskeletal) pain

Tell your healthcare provider about any side effect that bothers you or that does not go away. These are not all the possible side effects of BKEMV. For more information, ask your doctor or pharmacist.
Call your doctor for medical advice about side effects.
You may report side effects to FDA at 1-800-FDA-1088.

General information about the safe and effective use of BKEMV.
Medicines are sometimes prescribed for purposes other than those listed in a Medication Guide. You can ask your pharmacist or healthcare provider for information about BKEMV that is written for health professionals.

What are the ingredients in BKEMV?
Active ingredient: eculizumab-aeeb
Inactive ingredients: sorbitol (E420), acetic acid, polysorbate 80 (vegetable origin), edetate disodium (EDTA), sodium hydroxide may be added to adjust pH, and Water for Injection, USP.

BKEMV® (eculizumab-aeeb)
Manufactured by:
Amgen Inc.
One Amgen Center Drive
Thousand Oaks, CA 91320-1799 U.S.A.
U.S. License Number 1080
© 2024 – 2025 Amgen Inc. All rights reserved.
1xxxxxx v3

This Medication Guide has been approved by the U.S. Food and Drug Administration.

Revised 11/2025

PRINCIPAL DISPLAY PANEL - 30 mL Vial Carton

300
mg/30 mL

BKEMV™
(eculizumab-aeeb)
Injection

NDC 55513-180-01

300 mg/30 mL
(10 mg/mL)

For Intravenous Infusion Only
ATTENTION: Enclosed Medication Guide is
required for each patient.
Sterile Solution - No Preservative

Must be diluted prior to use.
Contains 1 Single-Dose Vial
Discard unused portion.

AMGEN®

Rx Only